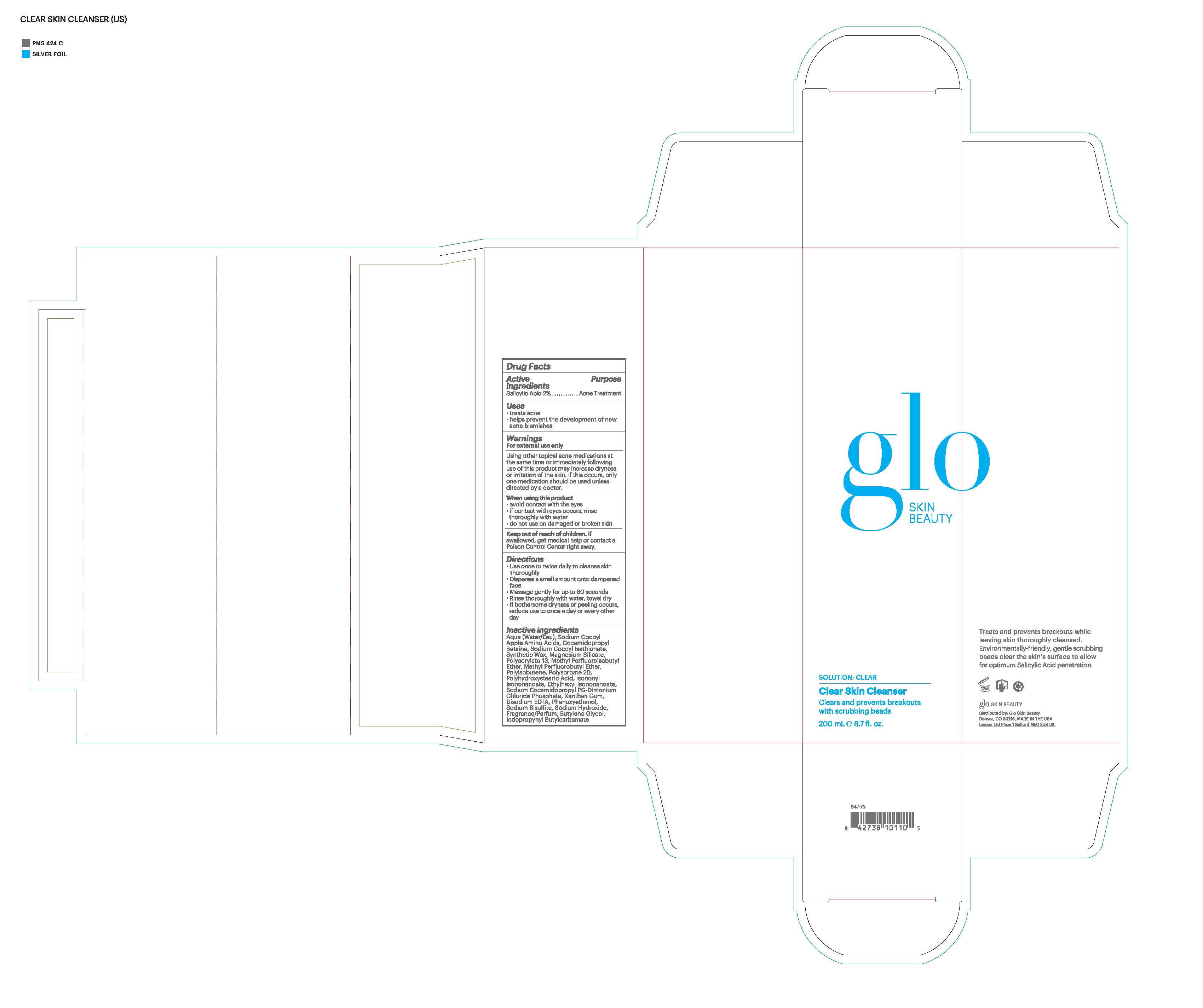 DRUG LABEL: glo SKIN BEAUTY Clear Skin Cleanser
NDC: 60541-1700 | Form: LIQUID
Manufacturer: Hayden Caleel LLC
Category: otc | Type: HUMAN OTC DRUG LABEL
Date: 20250105

ACTIVE INGREDIENTS: SALICYLIC ACID 2 g/100 g
INACTIVE INGREDIENTS: SODIUM COCO-SULFATE; COCAMIDOPROPYL BETAINE; SODIUM COCOYL ISETHIONATE; SYNTHETIC WAX (1200 MW); MAGNESIUM SILICATE; SODIUM POLYACRYLATE (8000 MW); METHYL PERFLUOROISOBUTYL ETHER; METHYL PERFLUOROBUTYL ETHER; POLYISOBUTYLENE (1000 MW); POLYSORBATE 20; POLYHYDROXYSTEARIC ACID (2300 MW); ISONONYL ISONONANOATE; ETHYLHEXYL ISONONANOATE; XANTHAN GUM; DISODIUM EDTA-COPPER; PHENOXYETHANOL; SODIUM BISULFITE; SODIUM HYDRIDE; BUTYLENE GLYCOL; IODOPROPYNYL BUTYLCARBAMATE

DRUG FACTS

Active Ingredients

Salicylic Acid 2%

Purpose

Acne Treatment

Uses

- Treats Acne
- Helps prevent the development of new acne blemishes

Warnings

Using other topical acne medications at the same tiem or immediatly following use of this prouct may increase dryness or irritation of the skin. If this occurs, only one medication shoul be used unless directed by a doctor.

For external use only
When using this product
• avoid contact with the eyes
• if contact occurs, rinse thoroughly with water
• do not use on damaged or broken skin

Keep out of reach of children. If swallowed, get medical help
or contact a Poison Control Center right away.

Directions

- Use once or twice daily to cleanse skin thoroughly
- Dispense a small amount onto dampened face
- Massage gently for up to 60 seconds
- Rinse thoroughly with water, towel dry
- If bothersome dryness or peeling occurs, reduce use to once a day or every other ay

Inactive Ingredients

Aqua/Water/Eau, Sodium Cocoyl Apple Amino Acids, Cocamidopropyl Betaine, Sodium Cocoyl Isethionate, Synthetic Wax, Magnesium Silicate, Polyacrylate-13, Methyl Perfluoroisobutyl Ether, Methyl Perfluorobutyl Ether, Polyisobutene, Polysorbate 20, Polyhydroxystearic Acid, Isononyl Isononanoate, Ethylhexyl Isononanoate, Sodium Cocamidopropyl PG-Dimonium Chloride Phosphate, Xanthan Gum, Disodium EDTA, Phenoxyethanol, Sodium Bisulfite, Sodium Hydroxide, Parfum/Fragrance, Butylene Glycol, Iodopropynyl Butylcarbamate, Limonene